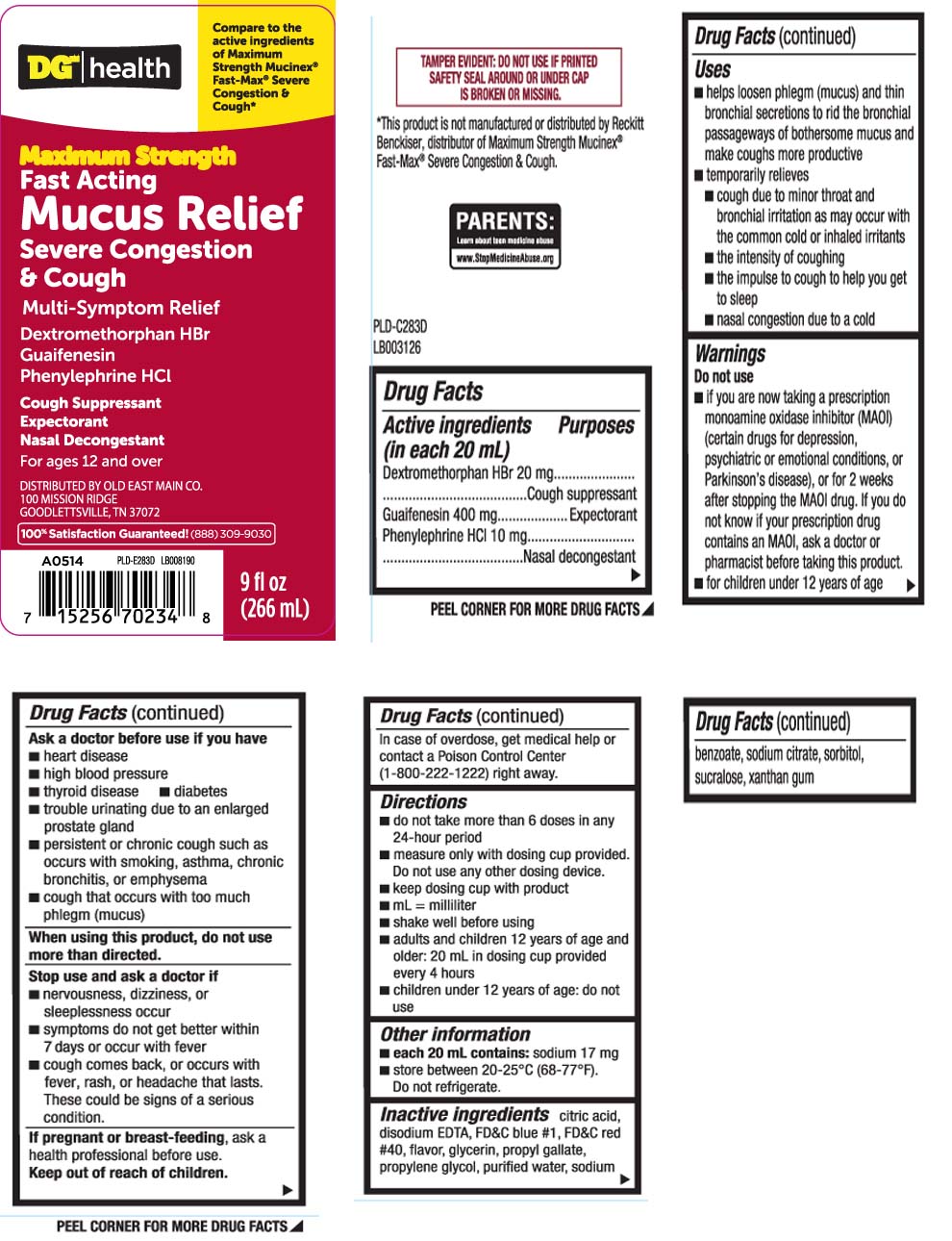 DRUG LABEL: Fast Acting Mucus Relief
NDC: 55910-037 | Form: LIQUID
Manufacturer: Dolgencorp, Inc.  (DOLLAR GENERAL & REXALL)
Category: otc | Type: HUMAN OTC DRUG LABEL
Date: 20251111

ACTIVE INGREDIENTS: DEXTROMETHORPHAN HYDROBROMIDE 20 mg/20 mL; GUAIFENESIN 400 mg/20 mL; PHENYLEPHRINE HYDROCHLORIDE 10 mg/20 mL
INACTIVE INGREDIENTS: ANHYDROUS CITRIC ACID; EDETATE DISODIUM; FD&C BLUE NO. 1; FD&C RED NO. 40; GLYCERIN; PROPYL GALLATE; PROPYLENE GLYCOL; WATER; SODIUM BENZOATE; TRISODIUM CITRATE DIHYDRATE; SORBITOL; SUCRALOSE; XANTHAN GUM

Drug Facts

Active ingredients (in each 20 mL)

Dextromethorphan HBr 20 mg

Guaifenesin 400 mg

Phenylephrine HCl 10 mg

Purposes

Cough suppressant

Expectorant

Nasal decongestant

Uses

- helps loosen phlegm (mucus) and thin bronchial secretions to rid the bronchial passageways of bothersome mucus and make coughs more productive
- temporarily relieves:
  - cough due to minor throat and bronchial irritation as may occur with the common cold or inhaled irritants
  - the intensity of coughing
  - the impulse to cough to help you get to sleep
  - nasal congestion due to a cold

Warnings

Do not use

- for children under 12 years of age
- if you are now taking a prescription monoamine oxidase inhibitor (MAOI) (certain drugs for depression, psychiatric or emotional conditions, or Parkinson's disease), or for 2 weeks after stopping the MAOI drug. If you do not know if your prescription drug contains an MAOI, ask a doctor or pharmacist before taking this product.

Ask a doctor before use if you have

- heart disease
- thyroid disease
- diabetes
- high blood pressure
- trouble urinating due to an enlarged prostate gland
- persistent or chronic cough such as occurs with smoking, asthma, chronic bronchitis or emphysema
- cough that occurs with too much phlegm (mucus)

When using this product,

do not use more than directed

Stop use and ask a doctor if

- nervousness, dizziness or sleeplessness occur
- symptoms do not get better within 7 days or occur with fever
- cough comes back, or occurs with rash or persistent headache. These could be signs of a serious condition.

If pregnant or breast-feeding,

ask a health professional before use.

Keep out of reach of children.

In case of overdose, get medical help or contact a Poison Control Center (1-800-222-1222) right away.

Directions

- do not take more than 6 doses in a 24-hour period
- measure only with dosing cup provided. Do not use any other dosing device.
- keep dosing cup with product
- mL = milliliter
- shake well before using
- adults and children 12 years of age and older: 20 mL in dosing cup provided every 4 hours
- children under 12 years of age: do not use

Other information

- each 20 mL contains:sodium 17 mg
- store between 20-25ºC (68-77ºF). Do not refrigerate

Inactive ingredients

citric acid, disodium EDTA, FD&C blue #1, FD&C red #40, flavor, glycerin, propyl gallate, propylene glycol, purified water, sodium benzoate, sorbitol, sucralose, sodium citrate, xanthan gum

Principal Display Panel

Compare to the active ingredients of Maximum Strength Mucinex® Fast-Max® Severe Congestion & Cough*

Maximum Strength

Fast-Acting

Mucus Relief

Severe Cough & Congestion

Multi-Symptom Relief

Dextromethorphan HBr

Guaifenesin

Phenylephrine HCl

Cough suppressant

Expectorant

Nasal decongestant

fl oz (mL)

For ages 12 and over

*This product is not manufactured or distributed by Reckitt Benckiser, distributor of Maximum Strength Mucinex® Fast-Max® Severe Congestion & Cough

TAMPER EVIDENT: DO NOT USE IF PRINTED SAFETY SEAL AROUNG OR UNDER CAP IS BROKEN OR MISSING.

DISTRIBUTED BY OLD EAST MAIN CO.

100 MISSION RIDGE,

GOODLETTSVILLE, TN 37072

Package Label

DOLLAR GENERAL HEALTH Maximum Strength Mucus Relief